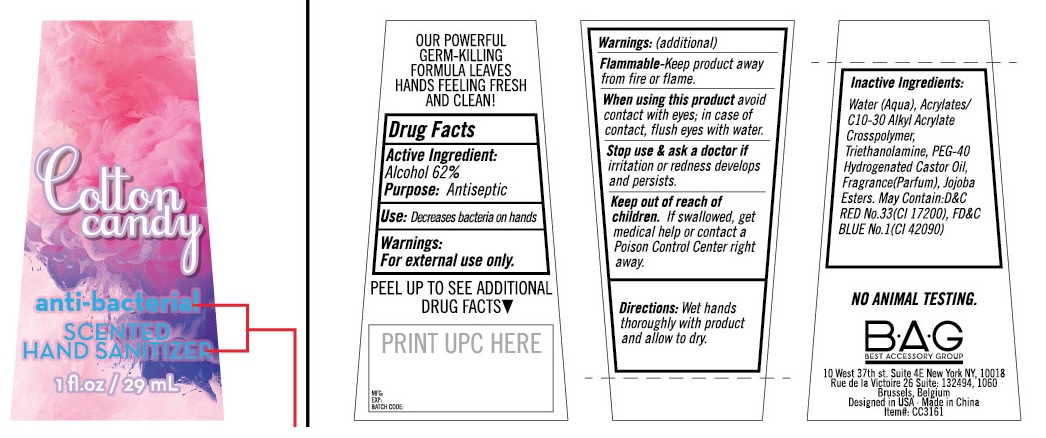 DRUG LABEL: Cotton candy anti-bacterial SCENTED HAND SANITIZER
NDC: 60533-003 | Form: SOLUTION
Manufacturer: Best Accessory Group
Category: otc | Type: HUMAN OTC DRUG LABEL
Date: 20130813

ACTIVE INGREDIENTS: ALCOHOL 62 mL/100 mL
INACTIVE INGREDIENTS: WATER; CARBOMER COPOLYMER TYPE A (ALLYL PENTAERYTHRITOL CROSSLINKED); TROLAMINE; POLYOXYL 40 HYDROGENATED CASTOR OIL; ETHYL JOJOBATE; D&C RED NO. 33; FD&C BLUE NO. 1

Cotton candy anti-bacterial SCENTED HAND SANITIZER

OUR POWERFUL GERM-KILLING FORMULA LEAVES HANDS FEELING FRESH AND CLEAN !

Drug Facts

Active Ingredient:

Alcohol 62%

Purpose: Antiseptic

INDICATIONS AND USAGE

Use: Decreases bacteria on hands.

Warnings:

For External Use Only.

WHEN USING

Flammable -Keep product away from fire or flame.

When using this product avoid contact with eyes; in case of contact, flush eyes with water.

STOP USE

Stop use & ask a doctor if irritation or redness develops and persists.

Keep out of reach of children. If swallowed, get medical help or contact a Poison Control Center right away.

DOSAGE AND ADMINISTRATION

Directions: Wet hands thoroughly with product and allow to dry.

Inactive Ingredients:

Water(Aqua), Acrylates/C10-30 Alkyl Acrylate Crosspolymer,Triethanolamine, PEG-40 Hydrogenated Castor Oil, Fragrance (Perfume), Jojoba Esters. May Contain: D&C RED No.33 (CI 17200), FD&C BLUE No. 1 (CI 42090)

NO ANIMAL TESTING

B•A•G

BEST ACCESSORY GROUP

10 West 37th st. Suite 4E New York NY, 10018
Rue de la Victoire 26 Suite: 132494, 1060
Brussels, Belgium
Designed in USA. Made in China
Item#: CC3161

PRINCIPAL DISPLAY PANEL - 29 mL Bottle Label

Cotton
candy

antibacterial

SCENTED
HAND SANITIZER

1 fl.oz - 29 mL